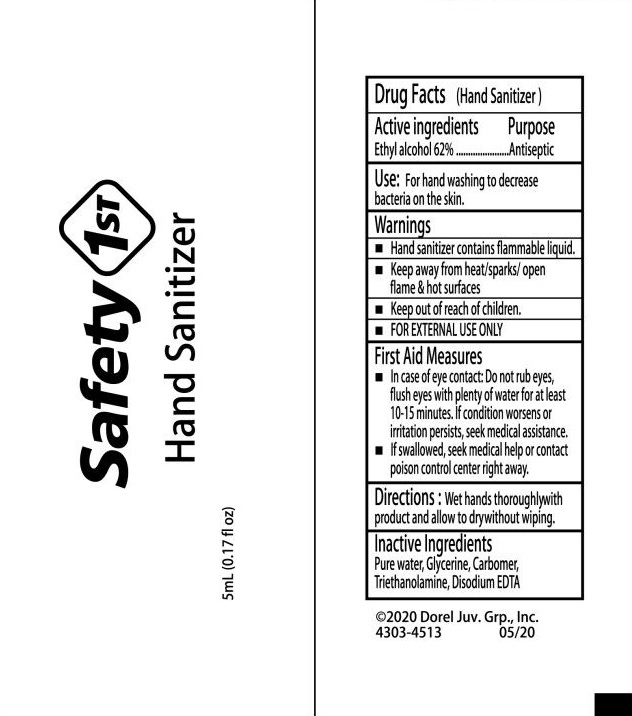 DRUG LABEL: Safety 1st hand sanitizer
NDC: 71734-318 | Form: LIQUID
Manufacturer: JIANGMEN SHUIZIRUN SANITARY ARTICLES CO., LTD.
Category: otc | Type: HUMAN OTC DRUG LABEL
Date: 20200701

ACTIVE INGREDIENTS: ALCOHOL 62 mL/100 mL
INACTIVE INGREDIENTS: GLYCERIN; CARBOMER 934; WATER; TROLAMINE; EDETATE DISODIUM

Drug Fact

Active Ingredient

Ethyl Alcohol 62%

Purpose

Antiseptic

Uses

- For hand washing to decrease bacteria and germs on the skin

Warnings

For external use only.

Hand sanitizer contains flammable liquid.

Keep away from heat/sparks/open flame and hot surfaces

WHEN USING

First aid measures

- In case of eye contact: Do not rub eyes, flush eye with plenty of water for at least 10-15 minutes. If condition worsens or irritation persists, seek medical assistanc.
- If swallowed, seek meical help or contact poison control center right away.

Keep out of reach of children.

keep out of readh of children.

Directions

Wet hands thoroughly with product and allow to dry without wiping.

Inactive Ingredients

Purified water, Glycerine, Carbomer, Triethanolamine, Disodium EDTA